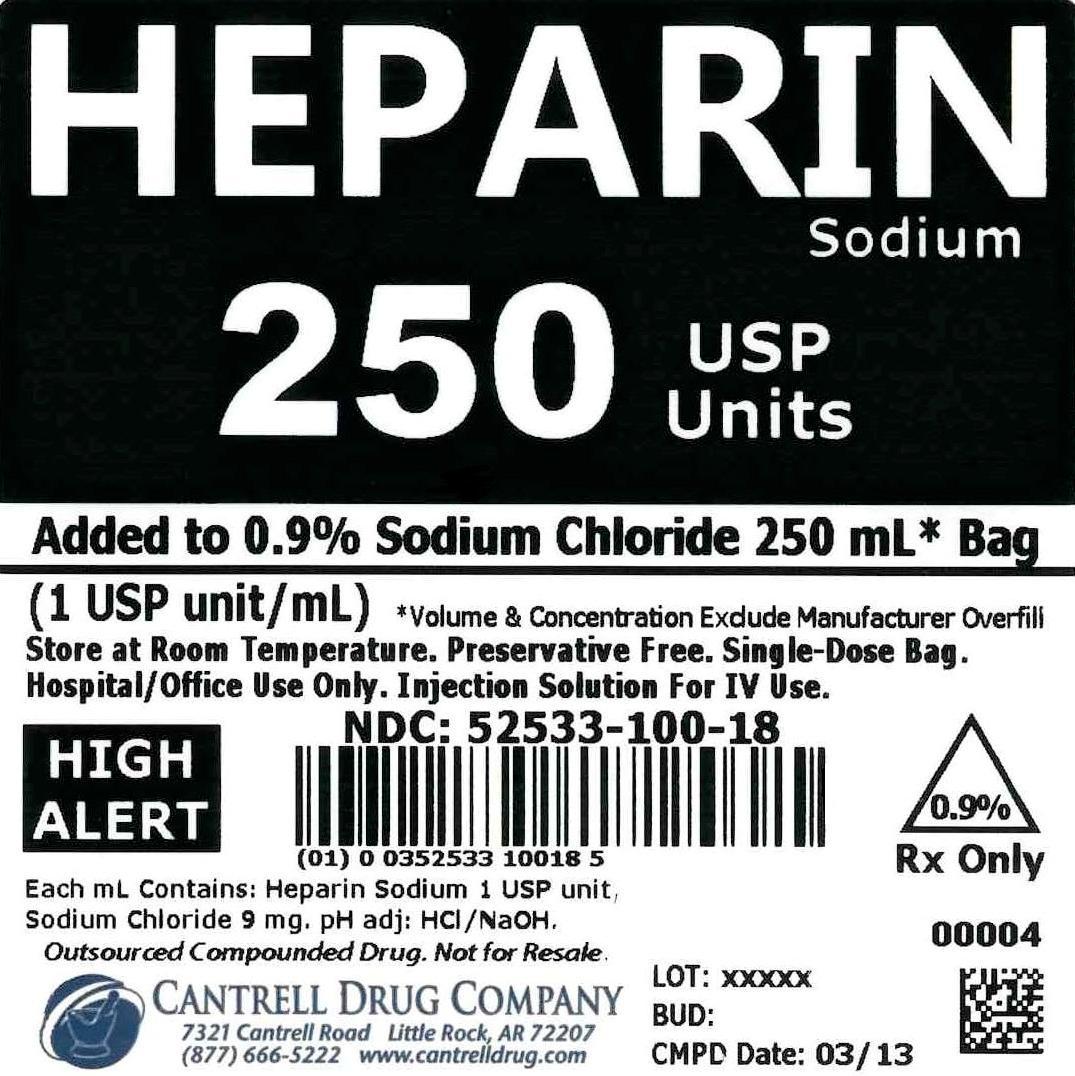 DRUG LABEL: Heparin Sodium
NDC: 52533-100 | Form: INJECTION, SOLUTION
Manufacturer: Cantrell Drug Company
Category: prescription | Type: HUMAN PRESCRIPTION DRUG LABEL
Date: 20141211

ACTIVE INGREDIENTS: Heparin Sodium 1 [USP'U]/1 mL
INACTIVE INGREDIENTS: SODIUM CHLORIDE 9 mg/1 mL; Water

Heparin Sodium 250 USP Units Added to 0.9% Sodium Chloride 250 mL Bag